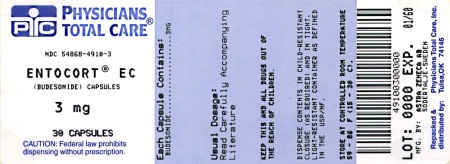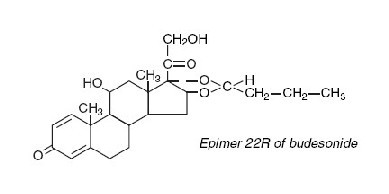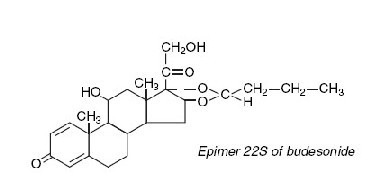 DRUG LABEL: ENTOCORT
NDC: 54868-4910 | Form: CAPSULE
Manufacturer: Physicians Total Care, Inc.
Category: prescription | Type: HUMAN PRESCRIPTION DRUG LABEL
Date: 20120207

ACTIVE INGREDIENTS: BUDESONIDE 3 mg/1 1
INACTIVE INGREDIENTS: ACETYLTRIBUTYL CITRATE; METHACRYLIC ACID; TRIETHYL CITRATE; POLYSORBATE 80; TALC; GELATIN; FERROSOFERRIC OXIDE; TITANIUM DIOXIDE; COLLOIDAL SILICON DIOXIDE; FERRIC OXIDE YELLOW; FERRIC OXIDE RED

ENTOCORT® EC
(budesonide)
CAPSULES

DESCRIPTION SECTION

Budesonide, the active ingredient of ENTOCORT® EC capsules, is a synthetic corticosteroid. It is designated chemically as (RS)-11β, 16α, 17,21-tetrahydroxypregna-1,4-diene-3,20-dione cyclic 16,17-acetal with butyraldehyde. Budesonide is provided as a mixture of two epimers (22R and 22S). The empirical formula of budesonide is C25H34O6 and its molecular weight is 430.5. Its structural formula is:

Budesonide is a white to off-white, tasteless, odorless powder that is practically insoluble in water and heptane, sparingly soluble in ethanol, and freely soluble in chloroform. Its partition coefficient between octanol and water at pH 5 is 1.6 x 10^3 ionic strength 0.01.

Each capsule contains 3 mg of micronized budesonide with the following inactive ingredients: ethylcellulose, acetyltributyl citrate, methacrylic acid copolymer type C, triethyl citrate, antifoam M, polysorbate 80, talc, and sugar spheres. The capsule shells have the following inactive ingredients: gelatin, iron oxide, and titanium dioxide.

CLINICAL PHARMACOLOGY

Budesonide has a high topical glucocorticosteroid (GCS) activity and a substantial first pass elimination. The formulation contains granules which are coated to protect dissolution in gastric juice, but which dissolve at pH >5.5, ie, normally when the granules reach the duodenum. Thereafter, a matrix of ethylcellulose with budesonide controls the release of the drug into the intestinal lumen in a time-dependent manner.

PHARMACOKINETICS

Absorption

The absorption of ENTOCORT EC seems to be complete, although Cmax and Tmax are variable. Time to peak concentration varies in individual patients between 30 and 600 minutes. Following oral administration of 9 mg of budesonide in healthy subjects, a peak plasma concentration of approximately 5 nmol/L is observed and the area under the plasma concentration time curve is approximately 30 nmol•hr/L. The systemic availability after a single dose is higher in patients with Crohn's disease compared to healthy volunteers, (21% vs 9%) but approaches that in healthy volunteers after repeated dosing.

Distribution

The mean volume of distribution (Vss) of budesonide varies between 2.2 and 3.9 L/kg in healthy subjects and in patients. Plasma protein binding is estimated to be 85 to 90% in the concentration range 1 to 230 nmol/L, independent of gender. The erythrocyte/plasma partition ratio at clinically relevant concentrations is about 0.8.

Metabolism

Following absorption, budesonide is subject to high first pass metabolism (80-90%). In vitro experiments in human liver microsomes demonstrate that budesonide is rapidly and extensively biotransformed, mainly by CYP3A4, to its 2 major metabolites, 6β-hydroxy budesonide and 16α-hydroxy prednisolone. The glucocorticoid activity of these metabolites is negligible (<1/100) in relation to that of the parent compound.

In vivo investigations with intravenous doses in healthy subjects are in agreement with the in vitro findings and demonstrate that budesonide has a high plasma clearance, 0.9-1.8 L/min. Similarly, high plasma clearance values have been shown in patients with Crohn’s disease. These high plasma clearance values approach the estimated liver blood flow, and, accordingly, suggest that budesonide is a high hepatic clearance drug.

The plasma elimination half-life, t1/2, after administration of intravenous doses ranges between 2.0 and 3.6 hours, and does not differ between healthy adults and patients with Crohn’s disease.

Excretion

Budesonide is excreted in urine and feces in the form of metabolites. After oral as well as intravenous administration of micronized [^3H]-budesonide, approximately 60% of the recovered radioactivity is found in urine. The major metabolites, including 6β-hydroxy budesonide and 16α-hydroxy prednisolone, are mainly renally excreted, intact or in conjugated forms. No unchanged budesonide is detected in urine.

Special Populations

No significant pharmacokinetic differences have been identified due to sex.

Hepatic Insufficiency

In patients with liver cirrhosis, systemic availability of orally administered budesonide correlates with disease severity and is, on average, 2.5-fold higher compared with healthy controls. Patients with mild liver disease are minimally affected. Patients with severe liver dysfunction were not studied. Absorption parameters are not altered, and for the intravenous dose, no significant differences in CL or Vss are observed.

Renal Insufficiency

The pharmacokinetics of budesonide in patients with renal impairment has not been studied. Intact budesonide is not renally excreted, but metabolites are to a large extent, and might therefore reach higher levels in patients with impaired renal function. However, these metabolites have negligible corticosteroid activity as compared with budesonide (<1/100). Thus, patients with impaired renal function taking budesonide are not expected to have an increased risk of adverse effects.

DRUG-DRUG INTERACTIONS

Budesonide is metabolized via CYP3A4. Potent inhibitors of CYP3A4 can increase the plasma levels of budesonide severalfold. Co-administration of ketoconazole results in an eight-fold increase in AUC of budesonide, compared to budesonide alone. Grapefruit juice, an inhibitor of gut mucosal CYP3A, approximately doubles the systemic exposure of oral budesonide. Conversely, induction of CYP3A4 can result in the lowering of budesonide plasma levels. Oral contraceptives containing ethinyl estradiol, which are also metabolized by CYP3A4, do not affect the pharmacokinetics of budesonide. Budesonide does not affect the plasma levels of oral contraceptives (ie, ethinyl estradiol).

Since the dissolution of the coating of ENTOCORT EC is pH dependent (dissolves at pH >5.5), the release properties and uptake of the compound may be altered after treatment with drugs that change the gastrointestinal pH. However, the gastric acid inhibitory drug omeprazole, 20 mg qd, does not affect the absorption or pharmacokinetics of ENTOCORT EC. When an uncoated oral formulation of budesonide is co-administered with a daily dose of cimetidine 1 g, a slight increase in the budesonide peak plasma concentration and rate of absorption occurs, resulting in significant cortisol suppression.

Food Effects

A mean delay in time to peak concentration of 2.5 hours is observed with the intake of a high-fat meal, with no significant differences in AUC.

PHARMACODYNAMICS

Budesonide has a high glucocorticoid effect and a weak mineralocorticoid effect, and the affinity of budesonide to GCS receptors, which reflects the intrinsic potency of the drug, is about 200-fold that of cortisol and 15-fold that of prednisolone.

Treatment with systemically active GCS is associated with a suppression of endogenous cortisol concentrations and an impairment of the hypothalamus-pituitary-adrenal (HPA) axis function. Markers, indirect and direct, of this are cortisol levels in plasma or urine and response to ACTH stimulation.

Plasma cortisol suppression was compared following five days’ administration of ENTOCORT EC capsules and prednisolone in a crossover study in healthy volunteers. The mean decrease in the integrated 0-24 hour plasma cortisol concentration was greater (78%) with prednisolone 20 mg/day compared to 45% with ENTOCORT EC 9 mg/day.

CLINICAL STUDIES

The safety and efficacy of ENTOCORT EC were evaluated in 994 patients with mild to moderate active Crohn’s disease of the ileum and/or ascending colon in 5 randomized and double-blind studies. The study patients ranged in age from 17 to 85 (mean 35), 40% were male and 97% were white. Of the 651 patients treated with ENTOCORT EC, 17 (2.6%) were ≥65 years of age and none were >74 years of age. The Crohn’s Disease Activity Index (CDAI) was the main clinical assessment used for determining efficacy in these 5 studies. The CDAI is a validated index based on subjective aspects rated by the patient (frequency of liquid or very soft stools, abdominal pain rating and general well-being) and objective observations (number of extraintestinal symptoms, need for antidiarrheal drugs, presence of abdominal mass, body weight and hematocrit). Clinical improvement, defined as a CDAI score of ≤150 assessed after 8 weeks of treatment, was the primary efficacy variable in these 5 comparative efficacy studies of ENTOCORT EC capsules. Safety assessments in these studies included monitoring of adverse experiences. A checklist of potential symptoms of hypercorticism was used.

One study (Study 1) compared the safety and efficacy of ENTOCORT EC 9 mg qd in the morning to a comparator. At baseline, the median CDAI was 272. ENTOCORT EC 9 mg qd resulted in a significantly higher clinical improvement rate at Week 8 than the comparator (Table 1).

Table 1 Clinical Improvement Rates (CDAI≤150) After 8 weeks of Treatment
Clinical Study | ENTOCORT EC
Clinical Study | 9 mg QD | 4.5 mg BID | Comparator [This drug is not approved for the treatment of Crohn's disease in the United States] | Placebo | Prednisolone
1 | 62/91 (69%) |  | 37/83 (45%)
2 |  | 31/61 (51%) |  | 13/64 (20%)
3 | 38/79 (48%) | 41/78 (53%) |  | 13/40 (33%)
4 | 35/58 (60%) | 25/60 (42%) |  |  | 35/58 (60%)
5 | 45/86 (52%) |  |  |  | 56/85 (65%)

Two placebo-controlled clinical trials (Studies 2 and 3) were conducted. Study 2 involved 258 patients and tested the effects of graded doses of ENTOCORT EC (1.5 mg bid, 4.5 mg bid, or 7.5 mg bid) versus placebo. At baseline, the median CDAI was 290. The 3 mg per day dose level (data not shown) could not be differentiated from placebo. The 9 mg per day arm was statistically different from placebo (Table 1), while no additional benefit was seen when the daily ENTOCORT EC dose was increased to 15 mg per day (data not shown). In Study 3, the median CDAI at baseline was 263. Neither 9 mg qd nor 4.5 mg bid ENTOCORT EC dose levels was statistically different from placebo (Table 1).

Two clinical trials (Studies 4 and 5) compared ENTOCORT EC capsules with oral prednisolone (initial dose 40 mg per day). At baseline, the median CDAI was 277. Equal clinical improvement rates (60%) were seen in the ENTOCORT EC 9 mg qd and the prednisolone groups in Study 4. In Study 5, 13% fewer patients in the ENTOCORT EC group experience clinical improvement than in the prednisolone group (no statistical difference) (Table 1).

The proportion of patients with normal plasma cortisol values (≥150 nmol/L) was significantly higher in the ENTOCORT EC groups in both trials (60 to 66%) than in the prednisolone groups (26 to 28%) at Week 8.

The efficacy and safety of ENTOCORT EC for maintenance of clinical remission were evaluated in four double-blind, placebo-controlled, 12-month trials in which 380 patients were randomized and treated once daily with 3 mg or 6 mg ENTOCORT EC or placebo. Patients ranged in age from 18 to 73 (mean 37) years. Sixty percent of the patients were female and 99% were Caucasian. The mean CDAI at entry was 96. Among the four clinical trials, approximately 75% of the patients enrolled had exclusively ileal disease. Colonoscopy was not performed following treatment. ENTOCORT EC 6 mg/day prolonged the time to relapse, defined as an increase in CDAI of at least 60 units to a total score >150 or withdrawal due to disease deterioration. The median time to relapse in the pooled population of the 4 studies was 154 days for patients taking placebo, and 268 days for patients taking ENTOCORT EC 6 mg/day. ENTOCORT EC 6 mg/day reduced the proportion of patients with loss of symptom control relative to placebo in the pooled population for the 4 studies at 3 months (28% vs. 45% for placebo).

INDICATIONS & USAGE

ENTOCORT EC is indicated for

- the treatment of mild to moderate active Crohn's disease involving the iluem and/or the ascending colon and
- the maintenance of clinical remission of mild to moderate Crohn's disease involving the ileum and/or the ascending colon for up to 3 months.

CONTRAINDICATIONS

ENTOCORT EC is contraindicated in patients with known hypersensitivity to budesonide.

WARNINGS

Glucocorticosteroids can reduce the response of the hypothalamus-pituitary-adrenal (HPA) axis to stress. In situations where patients are subject to surgery or other stress situations, supplementation with a systemic glucocorticosteroid is recommended. Since ENTOCORT EC is a glucocorticosteroid, general warnings concerning glucocorticoids should be followed.

Care is needed in patients who are transferred from glucocorticosteroid treatment with high systemic effects to corticosteroids with lower systemic availability, since symptoms attributed to withdrawal of steroid therapy, including those of acute adrenal suppression or benign intracranial hypertension, may develop. Adrenocortical function monitoring may be required in these patients and the dose of systemic steroid should be reduced cautiously.

Patients who are on drugs that suppress the immune system are more susceptible to infection than healthy individuals. Chicken pox and measles, for example, can have a more serious or even fatal course in susceptible patients or patients on immunosuppressant doses of glucocorticosteroids. In patients who have not had these diseases, particular care should be taken to avoid exposure. How the dose, route and duration of glucocorticosteroid administration affect the risk of developing a disseminated infection is not known. The contribution of the underlying disease and/or prior glucocorticosteroid treatment to the risk is also not known. If exposed, therapy with varicella zoster immune globulin (VZIG) or pooled intravenous immunoglobulin (IVIG), as appropriate, may be indicated. If exposed to measles, prophylaxis with pooled intramuscular immunoglobulin (IG) may be indicated. (See the respective package insert for complete VZIG and IG prescribing information.) If chicken pox develops, treatment with antiviral agents may be considered.

PRECAUTIONS

General

Caution should be taken in patients with tuberculosis, hypertension, diabetes mellitus, osteoporosis, peptic ulcer, glaucoma or cataracts, or with a family history of diabetes or glaucoma, or with any other condition where glucocorticosteroids may have unwanted effects.

Replacement of systemic glucocorticosteroids with ENTOCORT EC capsules may unmask allergies, eg, rhinitis and eczema, which were previously controlled by the systemic drug.

When ENTOCORT EC capsules are used chronically, systemic glucocorticosteroid effects such as hypercorticism and adrenal suppression may occur.

Reduced liver function affects the elimination of glucocorticosteroids, and increased systemic availability of oral budesonide has been demonstrated in patients with liver cirrhosis.

Information for Patients

ENTOCORT EC capsules should be swallowed whole and NOT CHEWED OR BROKEN.

Patients should be advised to avoid the consumption of grapefruit juice for the duration of their ENTOCORT EC therapy.

Patients should be given the patient package insert for additional information.

Drug Interactions

Concomitant oral administration of ketoconazole (a known inhibitor of CYP3A4 activity in the liver and in the intestinal mucosa) caused an eight-fold increase of the systemic exposure to oral budesonide. If treatment with inhibitors of CYP3A4 activity (such as ketoconazole, intraconazole, ritonavir, indinavir, saquinavir, erythromycin, etc.) is indicated, reduction of the budesonide dose should be considered. After extensive intake of grapefruit juice (which inhibits CYP3A4 activity predominantly in the intestinal mucosa), the systemic exposure for oral budesonide increased about two times. As with other drugs primarily being metabolized through CYP3A4, ingestion of grapefruit or grapefruit juice should be avoided in connection with budesonide administration.

Carcinogenesis, Mutagenesis, Impairment of Fertility

Carcinogenicity studies with budesonide were conducted in rats and mice. In a two-year study in Sprague-Dawley rats, budesonide caused a statistically significant increase in the incidence of gliomas in male rats at an oral dose of 50 mcg/kg (approximately 0.05 times the maximum recommended human dose on a body surface area basis). In addition, there were increased incidences of primary hepatocellular tumors in male rats at 25 mcg/kg (approximately 0.023 times the maximum recommended human dose on a body surface area basis) and above. No tumorigenicity was seen in female rats at oral doses up to 50 mcg/kg (approximately 0.05 times the maximum recommended human dose on a body surface area basis). In an additional two-year study in male Sprague-Dawley rats, budesonide caused no gliomas at an oral dose of 50 mcg/kg (approximately 0.05 times the maximum recommended human dose on a body surface area basis). However, it caused a statistically significant increase in the incidence of hepatocellular tumors at an oral dose of 50 mcg/kg (approximately 0.05 times the maximum recommended human dose on a body surface area basis). The concurrent reference corticosteroids (prednisolone and triamcinolone acetonide) showed similar findings. In a 91-week study in mice, budesonide caused no treatment-related carcinogenicity at oral doses up to 200 mcg/kg (approximately 0.1 times the maximum recommended human dose on a body surface area basis).

Budesonide was not genotoxic in the Ames test, the mouse lymphoma cell forward gene mutation (TK +/-) test, the human lymphocyte chromosome aberration test, the Drosophila melanogaster sex-linked recessive lethality test, the rat hepatocyte UDS test and the mouse micronucleus test.

In rats, budesonide had no effect on fertility at subcutaneous doses up to 80 mcg/kg (approximately 0.07 times the maximum recommended human dose on a body surface area basis). However, it caused a decrease in prenatal viability and viability in pups at birth and during lactation, along with a decrease in maternal body-weight gain, at subcutaneous doses of 20 mcg/kg (approximately 0.02 times the maximum recommended human dose on a body surface area basis) and above. No such effects were noted at 5 mcg/kg (approximately 0.005 times the maximum recommended human dose on a body surface area basis).

Pregnancy

Teratogenic Effects: Pregnancy Category C: As with other corticosteroids, budesonide was teratogenic and embryocidal in rabbits and rats. Budesonide produced fetal loss, decreased pup weights, and skeletal abnormalities at subcutaneous doses of 25 mcg/kg in rabbits (approximately 0.05 times the maximum recommended human dose on a body surface area basis) and 500 mcg/kg in rats (approximately 0.5 times the maximum recommended human dose on a body surface area basis).

There are no adequate and well-controlled studies in pregnant women. Budesonide should be used during pregnancy only if the potential benefit justifies the potential risk to the fetus.

Nonteratogenic Effects: Hypoadrenalism may occur in infants born of mothers receiving corticosteroids during pregnancy. Such infants should be carefully observed.

Nursing Mothers

The disposition of budesonide when delivered by inhalation from a dry powder inhaler at doses of 200 or 400 mcg twice daily for at least 3 months was studied in eight lactating women with asthma from 1 to 6 months postpartum.^1 Systemic exposure to budesonide in these women appears to be comparable to that in non-lactating women with asthma from other studies. Breast milk obtained over eight hours post-dose revealed that the maximum budesonide concentration for the 400 and 800 mcg total daily doses was 0.39 and 0.78 nmol/L, respectively, and occurred within 45 minutes after inhalation. The estimated oral daily dose of budesonide from breast milk to the infant is approximately 0.007 and 0.014 mcg/kg/day for the two dose regimens used in this study, which represents approximately 0.3% to 1% of the dose inhaled by the mother. Budesonide plasma concentrations obtained from five infants at about 90 minutes after breast feeding (and about 140 minutes after drug administration to the mother) were below quantifiable levels (<0.02 nmol/L in four infants and <0.04 nmol/L in one infant).

The recommended daily dose of ENTOCORT EC capsules is higher (up to 9 mg daily) compared with inhaled budesonide (up to 800 μg daily) given to mothers in the above study. The maximum budesonide plasma concentration following a 9 mg daily dose (in both single- and repeated-dose pharmacokinetic studies) of oral budesonide is approximately 5-10 nmol/L which is up to 10 times higher than the 1-2 nmol/L for a 800 μg daily dose of inhaled budesonide at steady state in the above inhalation study.

Since there are no data from controlled trials on the use of ENTOCORT EC by nursing mothers or their infants, and because of the potential for serious adverse reactions in nursing infants from ENTOCORT EC, a decision should be made whether to discontinue nursing or to discontinue ENTOCORT EC, taking into account the clinical importance of ENTOCORT EC to the mother.

Budesonide, like other corticosteroids, is secreted in human milk. Data from budesonide delivered via dry powder inhaler indicates that the total daily oral dose of budesonide available in breast milk to the infant is approximately 0.3% to 1% of the dose inhaled by the mother. Assuming the coefficient of extrapolation between the inhaled and oral doses is constant across all dose levels, at therapeutic doses of ENTOCORT EC, budesonide exposure to the nursing child may be up to 10 times higher than that by budesonide inhalation.

Pediatric Use

Safety and effectiveness in pediatric patients have not been established.

Geriatric Use

Clinical studies of ENTOCORT EC did not include sufficient numbers of subjects aged 65 and over to determine whether they respond differently from younger subjects. Other reported clinical experience has not identified differences in responses between the elderly and younger patients. In general, dose selection for an elderly patient should be cautious, usually starting at the low end of the dosing range, reflecting the greater frequency of decreased hepatic, renal, or cardiac function, and of concomitant disease or other drug therapy.

ADVERSE REACTIONS

Because clinical trials are conducted under widely varying conditions, adverse reaction rates observed in the clinical trials of a drug cannot be directly compared to rates in the clinical trials of another drug and may not reflect the rates observed in practice.

The safety of ENTOCORT EC was evaluated in 651 patients in five short-term, active disease state studies. They ranged in age from 17 to 74 (mean 35), 40% were male and 97% were white, 2.6% were ≥65 years of age. Five hundred and twenty patients were treated with ENTOCORT EC 9 mg (total daily dose). In general, ENTOCORT EC was well tolerated in these trials. The most common adverse events reported were headache, respiratory infection, nausea, and symptoms of hypercorticism. Clinical studies have shown that the frequency of glucocorticosteroid-associated adverse events was substantially reduced with ENTOCORT EC capsules compared with prednisolone at therapeutically equivalent doses. Adverse events occurring in ≥ 5% of the patients are listed in Table 2:

Table 2 Adverse Events Occurring in ≥5% of the Patients in any Treated Group
 | ENTOCORT EC; 9 mg; n=520 | Placebo; n=107 | Prednisolone; 40 mg; n=145 | Comparator; n=88
Adverse Event | Number (%) | Number (%) | Number (%) | Number (%)
Headache | 107 (21) | 19 (18) | 31 (21) | 11 (13)
Respiratory Infection | 55 (11) | 7 (7) | 20 (14) | 5 (6)
Nausea | 57 (11) | 10 (9) | 18 (12) | 7 (8)
Back Pain | 36 (7) | 10 (9) | 17 (12) | 5 (6)
Dyspepsia | 31 (6) | 4 (4) | 17 (12) | 3 (3)
Dizziness | 38 (7) | 5 (5) | 18 (12) | 5 (6)
Abdominal Pain | 32 (6) | 18 (17) | 6 (4) | 10 (11)
Flatulence | 30 (6) | 6 (6) | 12 (8) | 5 (6)
Vomiting | 29 (6) | 6 (6) | 6 (4) | 6 (7)
Fatigue | 25 (5) | 8 (7) | 11 (8) | 0 (0)
Pain | 24 (5) | 8 (7) | 17 (12) | 2 (2)

The safety of ENTOCORT EC was evaluated in 233 patients in four long-term clinical trials (52 weeks). A total of 145 patients were treated with ENTOCORT EC 6 mg. A total of 8% of ENTOCORT EC patients discontinued treatment due to adverse events compared with 10% in the placebo group. The adverse event profile in long-term treatment of Crohn’s disease was similar to that of short-term treatment with ENTOCORT EC 9 mg in active Crohn’s disease.

In the long-term clinical trials, the following adverse events occurred in ≥ 5% of the 6 mg ENTOCORT EC patients and are not listed in Table 2 or by body system below: diarrhea (10%); sinusitis (8%); infection viral (6%); and arthralgia (5%).

Adverse events occurring in 520 patients treated with ENTOCORT EC 9 mg (total daily dose) in five short-term, active disease state studies. with an incidence <5% and greater than placebo (n=107) are listed below by body system:

Body as a Whole: asthenia, C-Reactive protein increased, chest pain, dependent edema, face edema, flu-like disorder, malaise; Cardiovascular: hypertension; Central and Peripheral Nervous System: hyperkinesia, paresthesia, tremor, vertigo; Gastrointestinal: anus disorder, Crohn’s disease aggravated, enteritis, epigastric pain, gastrointestinal fistula, glossitis, hemorrhoids, intestinal obstruction, tongue edema, tooth disorder; Hearing and Vestibular: Ear infection-not otherwise specified; Heart Rate and Rhythm: palpitation, tachycardia; Metabolic and Nutritional: hypokalemia, weight increase; Musculoskeletal: arthritis aggravated, cramps, myalgia; Psychiatric: agitation, appetite increased, confusion, insomnia, nervousness, sleep disorder, somnolence; Resistance Mechanism: moniliasis; Reproductive, Female: intermenstrual bleeding, menstrual disorder; Respiratory: bronchitis, dyspnea; Skin and Appendages: acne, alopecia, dermatitis, eczema, skin disorder, sweating increased; Urinary: dysuria, micturition frequency, nocturia; Vascular: flushing; Vision: eye abnormality, vision abnormal; White Blood Cell: leukocytosis

For the 145 patients treated with ENTOCORT EC 6 mg (total daily dose) in long-term studies, the following adverse events that are not included in the list above occurred with an incidence <5% but >2% and greater than for placebo: abscess, amnesia, dizziness, fever, pharynx disorder, purpura, rhinitis, and urinary tract infection.

Glucocorticosteroid Adverse Reactions

Table 3 displays the frequency and incidence of signs/symptoms of hypercorticism by active questioning of patients in short-term clinical trials.

Table 3 Summary and Incidence of Signs/Symptoms of Hypercorticism in Short-Term Studies
 | ENTOCORT EC 9 mg; n=427 | Placebo; n=107 | Prednisolone Taper 40 mg; n=145
Signs/Symptom | Number (%) | Number (%) | Number (%)
Acne | 63 (15) | 14 (13) | 33 (23) [Statistically significantly different from ENTOCORT EC 9 mg]
Bruising Easily | 63 (15) | 12 (11) | 13 (9)
Moon Face | 46 (11) | 4 (4) | 53 (37)
Swollen Ankles | 32 (7) | 6 (6) | 13 (9)
Hirsutism | 22 (5) | 2 (2) | 5 (3)
Buffalo Hump | 6 (1) | 2 (2) | 5 (3)
Skin Striae | 4 (1) | 2 (2) | 0 (0)

Table 4 displays the frequency and incidence of signs/symptoms of hypercorticism by active questioning of patients in long-term clinical trials.

Table 4: Summary and Incidence of Signs/Symptoms of Hypercorticism in Long-Term Studies
 | ENTOCORT EC 3 mg; n-88 | ENTOCORT EC 6 mg; n=145 | Placebo; n=143
Signs/Symptom | Number (%) | Number (%) | Number (%)
Bruising Easily; Acne; Moon Face; Hirsutism; Swollen Ankles; Buffalo Hump; Skin Striae | 4 (5); 4 (5); 3 (3); 2 (2); 2 (2); 1 (1); 2 (2) | 15 (10); 14 (10); 6 (4); 5 (3); 3 (2); 1 (1); 0 | 5 (4); 3 (2); 0; 1 (1); 3 (2); 0; 0

The incidence of signs/symptoms of hypercorticism as described above in long-term clinical trials was similar to that seen in the short-term clinical trials.

A randomized, open, parallel-group multicenter safety study specifically compared the effect of ENTOCORT EC (<9 mg/day) and prednisolone (<40 mg/day) on bone mineral density over 2 years when used at doses adjusted to disease severity. Bone mineral density decreased significantly less with ENTOCORT EC than with prednisolone in steroid-naïve patients, whereas no difference could be detected between treatment groups for steroid-dependent patients and previous steroid users. The incidence of treatment-emergent symptoms of hypercorticism was significantly higher with prednisolone treatment.

Postmarketing Experience

The following adverse reactions have been identified during postapproval use of ENTOCORT EC. Because these reactions are reported voluntarily from a population of uncertain size, it is not always possible to reliably estimate their frequency or establish a causal relationship to drug exposure.

Immune System Disorders: Anaphylactic reactions; Nervous System Disorders: Benign intracranial hypertension.

CLINICAL LABORATORY TEST FINDINGS

The following potentially clinically significant laboratory changes in clinical trials, irrespective of relationship to ENTOCORT EC, were reported in ≥1% of patients: hypokalemia, leukocytosis, anemia, hematuria, pyuria, erythrocyte sedimentation rate increased, alkaline phosphatase increased, atypical neutrophils, C-reactive protein increased, and adrenal insufficiency.

OVERDOSAGE

Reports of acute toxicity and/or death following overdosage of glucocorticosteroids are rare. Treatment consists of immediate gastric lavage or emesis followed by supportive and symptomatic therapy.

If glucocorticosteroids are used at excessive doses for prolonged periods, systemic glucocorticosteroid effects such as hypercorticism and adrenal suppression may occur. For chronic overdosage in the face of severe disease requiring continuous steroid therapy, the dosage may be reduced temporarily.

Single oral doses of 200 and 400 mg/kg were lethal in female and male mice, respectively. The signs of acute toxicity were decreased motor activity, piloerection and generalized edema.

DOSAGE & ADMINISTRATION

The recommended adult dosage for the treatment of mild to moderate active Crohn's disease involving the ileum and/or the ascending colon is 9 mg taken once daily in the morning for up to 8 weeks.

Repeated 8 week courses of ENTOCORT EC can be given for recurring episodes of active disease.

Following an 8 week course(s) of treatment for active disease and once the patient’s symptoms are controlled (CDAI <150), ENTOCORT EC 6 mg is recommended once daily for maintenance of clinical remission up to 3 months. If symptom control is still maintained at 3 months an attempt to taper to complete cessation is recommended. Continued treatment with ENTOCORT EC 6 mg for more than 3 months has not been shown to provide substantial clinical benefit.

Patients with mild to moderate active Crohn’s disease involving the ileum and/or ascending colon have been switched from oral prednisolone to ENTOCORT EC with no reported episodes of adrenal insufficiency. Since prednisolone should not be stopped abruptly, tapering should begin concomitantly with initiating ENTOCORT EC treatment.

Hepatic Insufficiency: Patients with moderate to severe liver disease should be monitored for increased signs and/or symptoms of hypercorticism. Reducing the dose of ENTOCORT EC capsules should be considered in these patients.

CYP3A4 inhibitors: If concomitant administration with ketoconazole, or any other CYP3A4 inhibitor, is indicated, patients should be closely monitored for increased signs and/or symptoms of hypercorticism. Reduction in the dose of ENTOCORT EC capsules should be considered.

ENTOCORT EC capsules should be swallowed whole and not chewed or broken.

HOW SUPPLIED

ENTOCORT EC 3 mg capsules are hard gelatin capsules with an opaque light grey body and an opaque pink cap, coded with ENTOCORT EC 3 mg on the capsule.

They are supplied as follows:

Bottles of 10 | NDC 54868-4910-0
Bottles of 30 | NDC 54868-4910-3
Bottles of 90 | NDC 54868-4910-1
Bottles of 100 | NDC 54868-4910-2

STORAGE AND HANDLING SECTION

Store at 25°C (77°F); excursions permitted to 15-30°C (59-86°F) [See USP Controlled Room Temperature].

Keep container tightly closed.

References

1. Fält A, Bengtsson T, Kennedy B, et al. Exposure of infants to budesonide through breast milk of asthmatic mothers. J. Allergy Clin Immunol. 2007;120(4):798-802.

ENTOCORT EC is a trademark of the AstraZeneca group of companies

PROMETHEUS is a trademark of Prometheus Laboratories Inc.

© AstraZeneca 2009

Manufactured by:

AstraZeneca AB

S-151 85 Södertälje, Sweden

Distributed by:

Prometheus Laboratories Inc.

San Diego, CA 92121

Product of Sweden

June 2009

Relabeling and Repackaging by:
Physicians Total Care, Inc.
Tulsa, Oklahoma 74146

PATIENT PACKAGE INSERT

ENTOCORT® EC (budesonide) Capsules

Read this information carefully before you begin treatment. Read the information you get whenever you get more medicine. There may be new information. This information does not take the place of talking with your doctor about your medical condition or your treatment. If you have any questions about ENTOCORT EC (EN-toe-cort EE-CEE), ask your health care provider (provider). Only your provider can determine if ENTOCORT EC is right for you.

What is ENTOCORT EC?

ENTOCORT EC is a medicine to treat mild to moderate Crohn’s disease in many people. However, it does not work for everyone who takes it. ENTOCORT EC is a nonsystemic corticosteroid, which means it works mainly in one area of the body. The medicine in ENTOCORT EC is released in the intestine. Therefore, it controls the symptoms of Crohn’s disease even though 90% of the drug does not go into the bloodstream. Because of this, it causes fewer severe side effects than other corticosteroids. (See the end of this Patient Information for information about Crohn’s disease.)

Who should not take ENTOCORT EC?

Do not take ENTOCORT EC if:

· you have had an allergic reaction to ENTOCORT EC or any of its ingredients

To help your provider decide if ENTOCORT EC is right for you, tell your provider:

· if you had an allergic reaction to any medicine in the past

· the names of all the prescription and nonprescription medicines you now take. Be sure to tell your provider if you take ketoconazole, which can affect processing of ENTOCORT EC by the liver, steroids such as prednisone, or any other drug that suppresses your immune system

· if you are pregnant, think you may be pregnant, or plan to get pregnant. Your provider will talk about whether ENTOCORT EC is right for you

· if you are breast feeding talk with your provider because ENTOCORT EC is carried in human milk and it may harm the baby. Your provider should tell you whether you should stop breast feeding to take ENTOCORT EC or should use another treatment.

· if you ever had liver problems. Liver problems affect the amount of ENTOCORT EC that stays in your system, and dosage may need to be changed

· if you are about to have surgery for any reason. Your dosage may need to be changed

· if you have chicken pox or measles, or any other condition that suppresses the immune system

· if you or anyone in your family has had diabetes or glaucoma

· if you ever had tuberculosis, high blood pressure, osteoporosis, ulcers, or cataracts.

How should I take ENTOCORT EC?

Take ENTOCORT EC in the morning. Swallow each ENTOCORT EC capsule whole. Do not open, chew, or crush ENTOCORT EC capsules. Your provider will tell you how long to take ENTOCORT EC.

What should I avoid while taking ENTOCORT EC?

Patients who take medicines that suppress the immune system, such as ENTOCORT EC, are more likely to get infections. Avoid people with infections. Also, if you never had chicken pox or measles, be careful to avoid people with these conditions. These conditions can be more serious if you get them while taking ENTOCORT EC.

While you are taking ENTOCORT EC, do not drink grapefruit juice regularly. Grapefruit juice can increase the amount of ENTOCORT EC in your blood. Other juices, like orange juice or apple juice, do not have this effect.

What are the side effects of ENTOCORT EC?

The most common side effects of ENTOCORT EC are headache, infection in your air passages (respiratory infection), nausea, and symptoms of hypercorticism (too much steroids in your body).

These symptoms include an increase in the size of the face and neck, acne, and bruising. Most symptoms of too much steroids in your body occur less often with ENTOCORT EC than with other steroids.

Call your provider right away if you notice itching, skin rash, fever, swelling of your face and neck, or trouble breathing while you are taking ENTOCORT EC. These may be signs that you are allergic to the medicine and you may need emergency medical help.

Switching from a systemic medicine, like prednisone, to a nonsystemic medicine, such as ENTOCORT EC, can cause allergies controlled by the systemic medicine to come back. These allergies may include eczema (a skin disease) or rhinitis (inflammation inside the nose).

Call your provider if:

· your Crohn’s disease symptoms worsen during treatment

· you notice any side effects or any other symptoms that concern you

These are not all the possible side effects of ENTOCORT EC. Ask your provider or pharmacist for a complete listing of all possible side effects of ENTOCORT EC.

What is Crohn’s disease?

Crohn’s disease is an inflammatory bowel disease. The inflammation caused by Crohn’s disease is usually found in a part of the small intestine called the ileum and in the large intestine (colon). It may also occur in any part of the gastrointestinal tract (digestive system) from the mouth to the anus (rectum). The cause of Crohn’s disease is not yet known.

There are many symptoms of Crohn’s disease. These include diarrhea, crampy abdominal (stomach area) pain, fever, and sometimes bleeding from the rectum. Appetite loss followed by weight loss may occur. There may also be redness and soreness of the eyes, joint pain, and sores on the skin. These symptoms may range from mild to severe.

There is no cure yet for Crohn’s disease. However, it is possible for the disease to quiet down (go into remission). During these periods of remission, there may be times when the symptoms get worse. In general, people with Crohn’s disease are able to lead productive lives.

General advice about prescription medicines

Medicines are sometimes prescribed for conditions that are not mentioned in patient information leaflets. Do not use ENTOCORT EC for a condition for which it was not prescribed. Do not give ENTOCORT EC to other people, even if they have the same symptoms you have. It may harm them. Keep ENTOCORT EC and all medicines out of the reach of children.

This leaflet summarizes the most important information about ENTOCORT EC. If you would like more information, talk with your provider. You can ask your pharmacist or provider for information about ENTOCORT EC that is written for health professionals. You can also visit the ENTOCORT EC Web site at (www.EntocortEC.com) or call the information center at AstraZeneca toll-free (1-800-237-8898).

ENTOCORT is a trademark of the AstraZeneca group of companies.

PROMETHEUS is a trademark of Prometheus Laboratories Inc.

© AstraZeneca 2009

Manufactured by:

AstraZeneca AB

S-151 85 Södertälje, Sweden

Distributed by:

Prometheus Laboratories Inc.

San Diego, CA 92121

Product of Sweden

June 2009